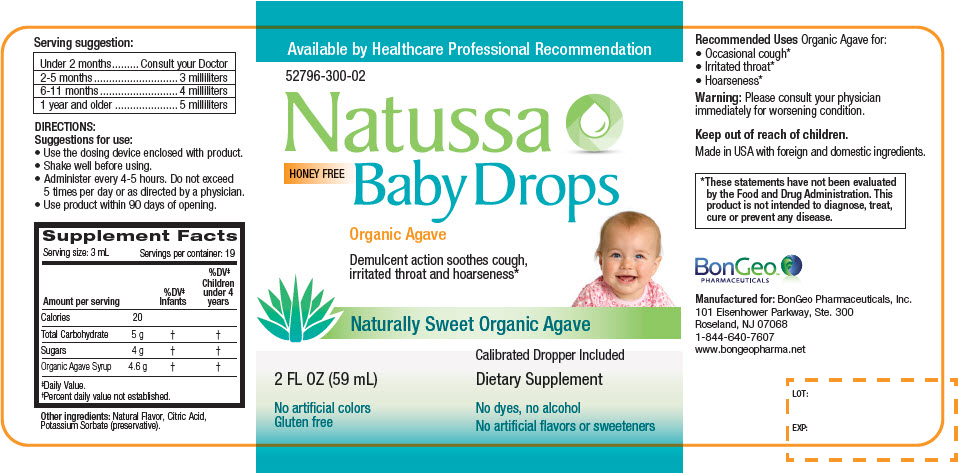 DRUG LABEL: Natussa Baby Drops
NDC: 52796-300 | Form: LIQUID
Manufacturer: BonGeo Pharmaceuticals
Category: other | Type: DIETARY SUPPLEMENT
Date: 20190131

ACTIVE INGREDIENTS: SUCROSE 4 g/3 mL; AGAVE AMERICANA STEM 4.6 g/3 mL
INACTIVE INGREDIENTS: CITRIC ACID MONOHYDRATE; POTASSIUM SORBATE

Natussa HONEY FREE Baby Drops

Serving suggestion

Under 2 months | Consult your Doctor
2-5 months | 3 milliliters
6-11 months | 4 milliliters
1 year and older | 5 milliliters

DIRECTIONS

Suggestions for use:

- Use the dosing device enclosed with product.
- Shake well before using.
- Administer every 4-5 hours. Do not exceed 5 times per day or as directed by a physician.
- Use product within 90 days of opening.

STATEMENT OF IDENTITY

Supplement Facts
Serving size: 3 mL | Servings per container: 19
Amount per serving |  | %DV [Daily Value.] Infants | %DV Children under 4 years
Calories | 20
Total Carbohydrate | 5 g | [Percent daily value not established.]
Sugars | 4 g
Organic Agave Syrup | 4.6 g

Other ingredients: Natural Flavor, Citric Acid, Potassium Sorbate (preservative).

Recommended Uses

Organic Agave for:

- Occasional cough [*These statements have not been evaluated by the Food and Drug Administration. This product is not intended to diagnose, treat, cure or prevent any disease.]
- Irritated throat
- Hoarseness

Warning

Please consult your physician immediately for worsening condition.

Keep out of reach of children.

HEALTH CLAIM

Made in USA with foreign and domestic ingredients.

HEALTH CLAIM

Manufactured for: BonGeo Pharmaceuticals, Inc.
101 Eisenhower Parkway, Ste. 300
Roseland, NJ 07068
1-844-640-7607
www.bongeopharma.net

LOT:

EXP:

PRINCIPAL DISPLAY PANEL - 59 mL Bottle Label

Available by Healthcare Professional Recommendation

52796-300-02

Natussa
HONEY FREE
Baby Drops

Organic Agave

Demulcent action soothes cough,
irritated throat and hoarseness*

Naturally Sweet Organic Agave

2 FL OZ (59 mL)

No artificial colors
Gluten free

Calibrated Dropper Included

Dietary Supplement

No dyes, no alcohol
No artificial flavors or sweeteners